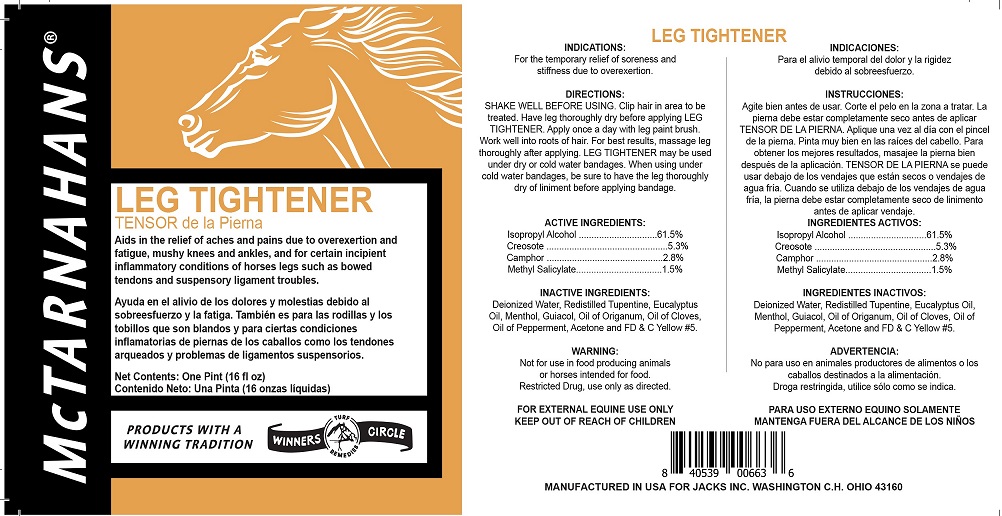 DRUG LABEL: LEG TIGHTENER
NDC: 61156-104 | Form: LINIMENT
Manufacturer: JACKS MFG INC
Category: animal | Type: OTC ANIMAL DRUG LABEL
Date: 20211208

ACTIVE INGREDIENTS: ISOPROPYL ALCOHOL 288.6375 mL/473.1762 mL; WOOD CREOSOTE 25 g/473.1762 mL; CAMPHOR, (-)- 13.6078 g/473.1762 mL; METHYL SALICYLATE 8.4052 g/473.1762 mL
INACTIVE INGREDIENTS: WATER 139.0192 mL/473.1762 mL; TURPENTINE 28.3906 mL/473.1762 mL; EUCALYPTUS OIL 9.4635 mL/473.1762 mL; MENTHOL 9.0718 g/473.1762 mL; GUAIACOL 0.0739 mL/473.1762 mL; ORIGANUM OIL 0.0739 mL/473.1762 mL; CLOVE OIL 0.0739 mL/473.1762 mL; PEPPERMINT OIL 0.2957 mL/473.1762 mL; ACETONE 0.03696 mL/473.1762 mL; FD&C YELLOW NO. 5 0.0133 mL/473.1762 mL

LEG TIGHTENER

INDICATIONS

For the temporary relief of soreness and stiffness due to overexertion.

DIRECTIONS

SHAKE WELL BEFORE USING.

Clip hair in area to be treated. Have leg thoroughly dry before applying LEG TIGHTENER.

Apply once a day with leg paint brush.

Work well into roots of hair. For best results, massage leg thoroughly after applying.

LEG TIGHTENER may be used under dry or cold water bandages.

When using under cold water bandages, be sure to have the leg thoroughly dry of liniment before applying bandage.

WARNING

Not for use in food producing animals or horses intended for food.

Restricted Drug, use only as directed.

FOR EXTERNAL EQUINE USE ONLY

KEEP OUT OF REACH OF CHILDREN